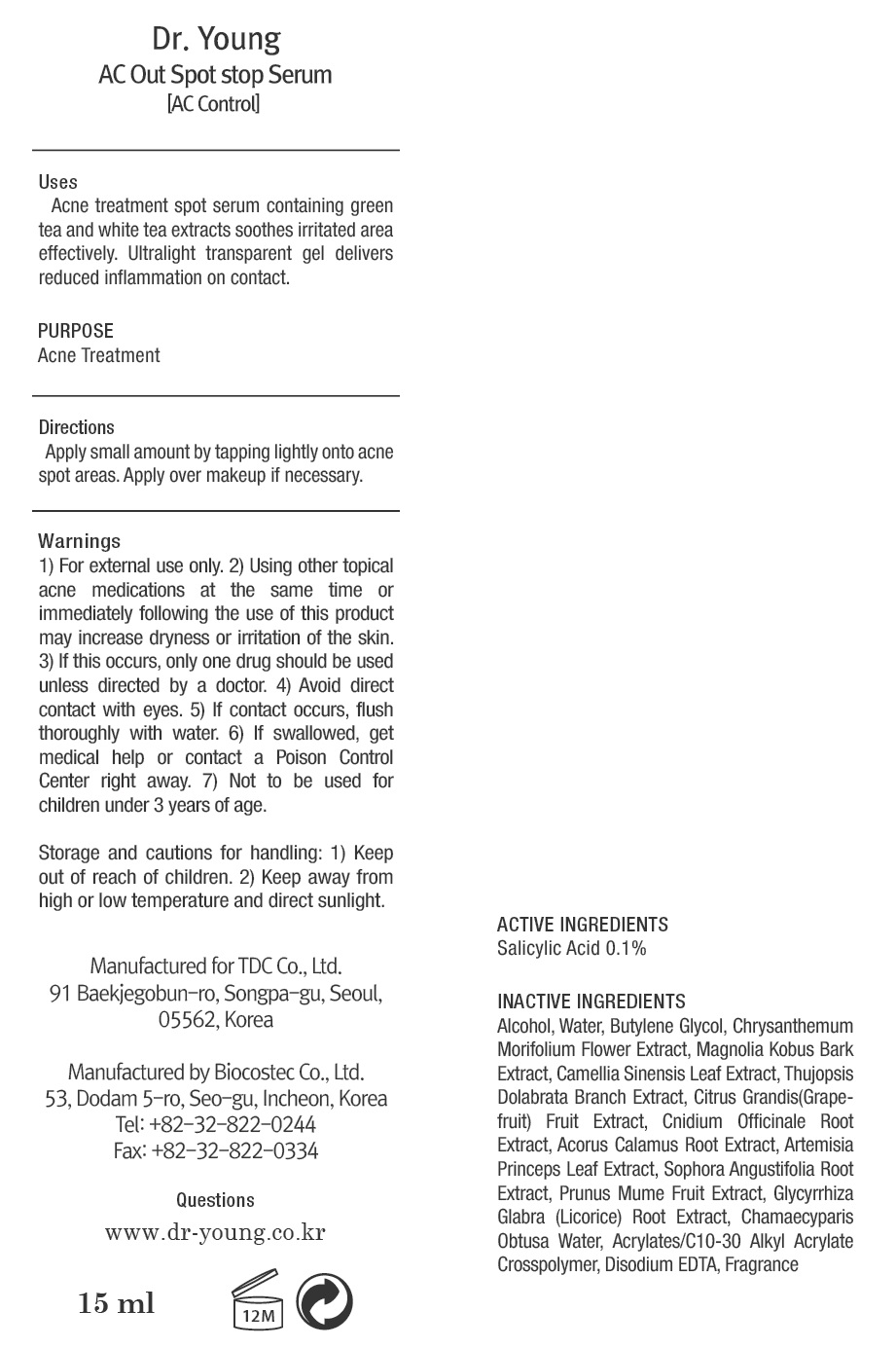 DRUG LABEL: Dr Young AC CONTROL AC Out Spot stop Serum
NDC: 43948-1340 | Form: CREAM
Manufacturer: Tdc, Co. Ltd
Category: otc | Type: HUMAN OTC DRUG LABEL
Date: 20181205

ACTIVE INGREDIENTS: Salicylic Acid 0.01 g/15 mL
INACTIVE INGREDIENTS: Alcohol; Water

ACTIVE INGREDIENT

Active ingredients: Salicylic Acid 0.1%

INACTIVE INGREDIENT

Inactive ingredients: Alcohol, Water, Butylene Glycol, Chrysanthemum Morifolium Flower Extract, Magnolia Kobus Bark Extract, Camellia Sinensis Leaf Extract, Thujopsis Dolabrata Branch Extract, Citrus Grandis(Grapefruit) Fruit Extract, Cnidium Officinale Root Extract, Acorus Calamus Root Extract, Artemisia Princeps Leaf Extract, Sophora Angustifolia Root Extract, Prunus Mume Fruit Extract, Glycyrrhiza Glabra (Licorice) Root Extract, Chamaecyparis Obtusa Water, Acrylates/C10-30 Alkyl Acrylate Crosspolymer, Disodium EDTA, Fragrance

PURPOSE

Purpose: Acne Treatment

WARNINGS

Warning: 1) For external use only. 2) Using other topical acne medications at the same time or immediately following the use of this product may increase dryness or irritation of the skin. 3) If this occurs, only one drug should be used unless directed by a doctor. 4) Avoid direct contact with eyes. 5) If contact occurs, flush thoroughly with water. 6) If swallowed, get medical help or contact a Poison Control Center right away. 7) Not to be used for children under 3 years of age.

Storage and cautions for handling: 1) Keep out of reach of children. 2) Keep away from high or low temperature and direct sunlight.

KEEP OUT OF REACH OF CHILDREN

Uses

Uses: Acne treatment spot serum containing green tea and white tea extracts soothes irritated area effectively. Ultralight transparent gel delivers reduced inflammation on contact.

Directions

Directions: Apply small amount by tapping lightly onto acne spot areas. Apply over makeup if necessary.